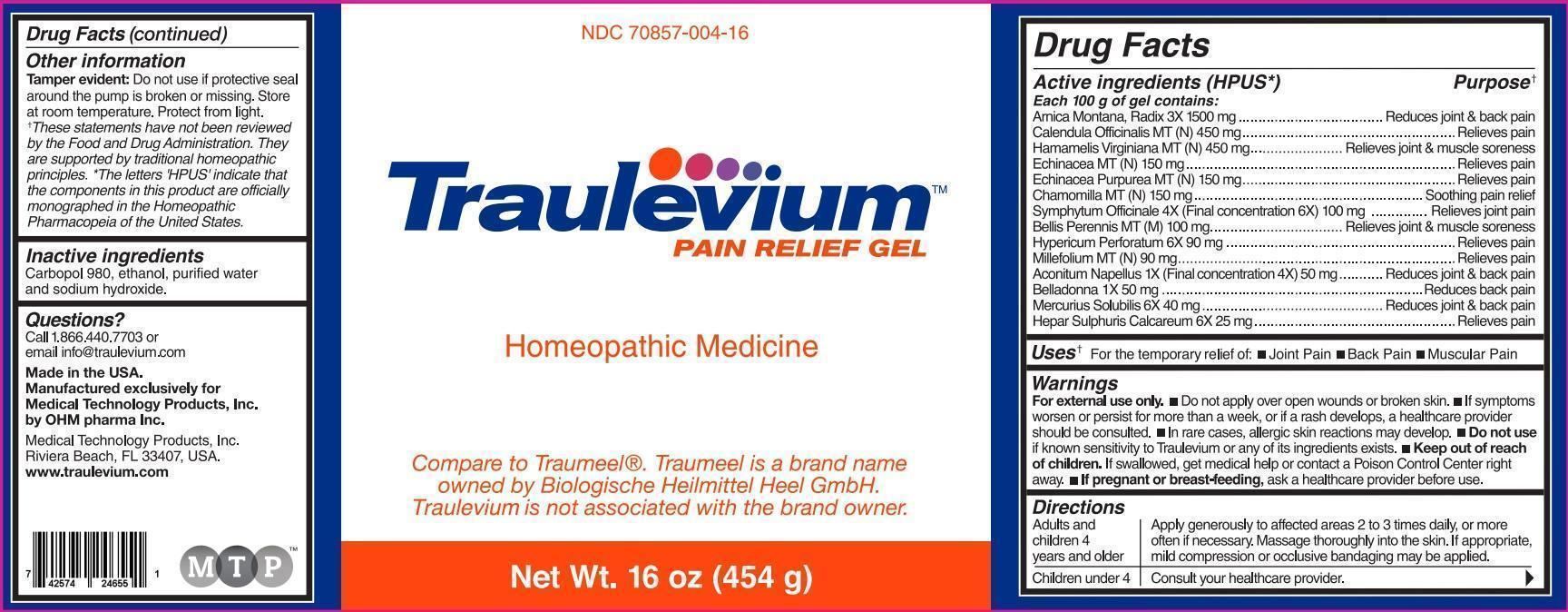 DRUG LABEL: Traulevium


NDC: 70857-004 | Form: GEL
Manufacturer: Medical Technology Products, Inc.
Category: homeopathic | Type: HUMAN OTC DRUG LABEL
Date: 20211229

ACTIVE INGREDIENTS: ARNICA MONTANA 3 [hp_X]/100 g; CALENDULA OFFICINALIS FLOWERING TOP 0.45 g/100 g; HAMAMELIS VIRGINIANA ROOT BARK/STEM BARK 0.45 g/100 g; ECHINACEA, UNSPECIFIED 0.15 g/100 g; ECHINACEA PURPUREA 0.15 g/100 g; MATRICARIA RECUTITA 0.15 g/100 g; COMFREY ROOT 6 [hp_X]/100 g; BELLIS PERENNIS 0.1 g/100 g; HYPERICUM PERFORATUM 6 [hp_X]/100 g; ACHILLEA MILLEFOLIUM 0.09 g/100 g; ACONITUM NAPELLUS 4 [hp_X]/100 g; ATROPA BELLADONNA 1 [hp_X]/100 g; MERCURIUS SOLUBILIS 6 [hp_X]/100 g; CALCIUM SULFIDE 6 [hp_X]/100 g
INACTIVE INGREDIENTS: WATER; ALCOHOL; SODIUM HYDROXIDE; CARBOMER HOMOPOLYMER TYPE C (ALLYL PENTAERYTHRITOL CROSSLINKED)

Traulevium Pain Relief Gel

ACTIVE INGREDIENTS

Active ingredients (HPUS*) | Purpose**
Each 100 g of gel contains:
Arnica Montana, Radix 3X 1500 mg | Reduces joint & back pain
Calendula Officinalis MT (N) 450 mg | Relieves pain
Hamamelis Virginiana MT (N) 450 mg | Relieves joint & muscle soreness
Echinacea MT (N) 150 mg | Relieves pain
Echinacea Purpurea MT (N) 150 mg | Relieves pain
Chamomilla MT (N) 150 mg | Soothing pain relief
Symphytum Officinale 4X (Final concentration 6X) 100 mg | Relieves joint pain
Bellis Perennis MT (M) 100 mg | Relieves joint & muscle soreness
Hypericum Perforatum 6X 90 mg | Relieves pain
Millefolium MT (N) 90 mg | Relieves pain
Aconitum Napellus 1X (Final concentration 4X) 50 mg | Reduces joint & back pain
Belladonna 1X 50 mg | Reduces back pain
Mercurius Solubilis 6X 40 mg | Reduces joint & back pain
Hepar Sulphuris Calcareum 6X 25 mg | Relieves pain

USES

Uses** For the temporary relief of:

- Joint Pain
- Back Pain
- Muscular Pain

WARNINGS

For external use only.

- Do not apply over open wounds or broken skin.
- If symptoms worsen or persist for more than a week, or if a rash develops, a healthcare provider should be consulted.
- In rare cases, allergic skin reactions may develop.
- Do not use if known sensitivity to Traulevium or any of its ingredients exists.
- Keep out of reach of children. If swallowed, get medical help or contact a Poison Control Center right away.
- If pregnant or breast-feeding, consult a healthcare provider before use.

Keep out of the reach of children.

DIRECTIONS

Adults and children 4 years and older | Apply generously to affected areas 2 to 3 times daily, or more often if necessary. Massage thoroughly into the skin. If appropriate, mild compression or occlusive bandaging may be applied.
Children under 4 | Consult your healthcare provider.

OTHER INFORMATION

Tamper evident: Do not use if protective seal around the pump is broken or missing. Store at room temperature. Protect from light.

**These statements have not been reviewed by the Food and Drug Administration. They are supported by traditional homeopathic principles.

*The letters 'HPUS' indicate that the components in this product are officially monographed in the Homeopathic Pharmacopeia of the United States.

INACTIVE INGREDIENTS

Carbopol 980, ethanol, purified water and sodium hydroxide.

QUESTIONS?

Call 1.866.440.7703 or e-mail info@traulevium.com

Made in the USA.

Manufactured exclusively for Medical Technology Products, Inc. by OHM pharma Inc.

Medical Technology Products, Inc.

Riviera Beach, FL 33407, USA.

www.traulevium.com

PACKAGE LABEL

NDC 70857-004-16

Traulevium™

Pain Relief Gel

Homeopathic Medicine

Compare to Traumeel®. Traumeel is a brand name owned by Biologische Heilmittel Heel GmbH. Traulevium is not associated with the brand owner.

Net Wt. 16oz (454 g)

PURPOSE

Pain Relief Gel